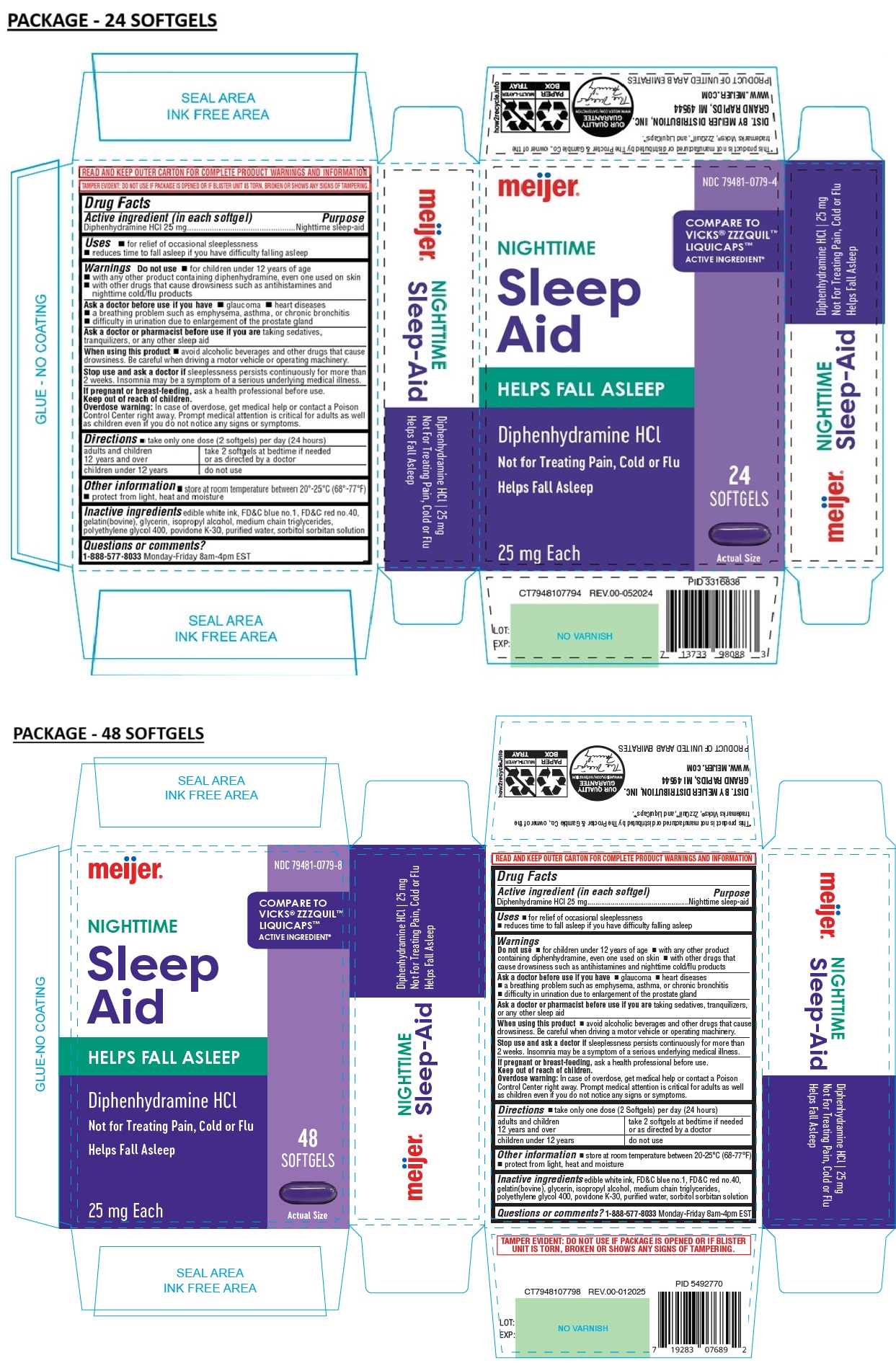 DRUG LABEL: meijer NIGHTTIME Sleep Aid SOFTGEL
NDC: 79481-0779 | Form: CAPSULE, LIQUID FILLED
Manufacturer: Meijer, Inc.
Category: otc | Type: HUMAN OTC DRUG LABEL
Date: 20250219

ACTIVE INGREDIENTS: DIPHENHYDRAMINE HYDROCHLORIDE 25 mg/1 1
INACTIVE INGREDIENTS: FD&C BLUE NO. 1; FD&C RED NO. 40; GELATIN TYPE B BOVINE (230 BLOOM); GLYCERIN; ISOPROPYL ALCOHOL; MEDIUM-CHAIN TRIGLYCERIDES; POLYETHYLENE GLYCOL 400; POVIDONE K30; WATER; SORBITOL; SORBITAN

meijer NIGHTTIME Sleep Aid SOFTGEL

Active ingredient (in each softgel)

Diphenhydramine HCl 25 mg

Purpose

Nighttime sleep-aid

Uses

• for relief of occasional sleeplessness
• reduces time to fall asleep if you have difficulty falling asleep

Warnings

Do not use • for children under 12 years of age
• with any other product containing diphenhydramine, even one used on skin
• with other drugs that cause drowsiness such as antihistamines and nighttime cold/flu products

Ask a doctor before use if you have • glaucoma • heart diseases
• a breathing problem such as emphysema, asthma, or chronic bronchitis
• difficulty in urination due to enlargement of the prostate gland

Ask a doctor or pharmacist before use if you are taking sedatives, tranquilizers, or any other sleep aid

When using this product • avoid alcoholic beverages and other drugs that cause drowsiness. Be careful when driving a motor vehicle or operating machinery.

Stop use and ask a doctor if sleeplessness persists continuously for more than 2 weeks. Insomnia may be a symptom of a serious underlying medical illness.

If pregnant or breast-feeding, ask a health professional before use.

Keep out of reach of children.
Overdose warning: In case of overdose, get medical help or contact a Poison Control Center right away. Prompt medical attention is critical for adults as well as children even if you do not notice any signs or symptoms.

Directions

• take only one dose (2 softgels) per day (24 hours)

adults and children 12 years and over | take 2 softgels at bedtime if needed or as directed by a doctor
children under 12 years | do not use

Other information

• store at room temperature between 20°-25°C (68°-77°F)
• protect from light, heat and moisture

Inactive ingredients

edible white ink, FD&C blue no.1, FD&C red no.40, gelatin(bovine), glycerin, isopropyl alcohol, medium chain triglycerides, polyethylene glycol 400, povidone K-30, purified water, sorbitol sorbitan solution

Questions or comments?

1-888-577-8033 Monday-Friday 8am-4pm EST

COMPARE TO VICKS® ZZZQUIL™ LIQUICAPS™ ACTIVE INGREDIENT*

HELPS FALL ASLEEP

Not for Treating Pain, Cold or Flu

READ AND KEEP OUTER CARTON FOR COMPLETE PRODUCT WARNINGS AND INFORMATION

TAMPER EVIDENT: DO NOT USE IF PACKAGE IS OPENED OR IF BLISTER UNIT IS TORN, BROKEN OR SHOWS ANY SIGNS OF TAMPERING.

*This product is not manufactured or distributed by The Procter & Gamble Co., owner of the trademarks Vicks®, ZzzQuil™, and LiquiCaps™.

DIST. BY MEIJER DISTRIBUTION, INC.
GRAND RAPIDS, MI 49544

WWW.MEIJER.COM

PRODUCT OF UNITED ARAB EMIRATES